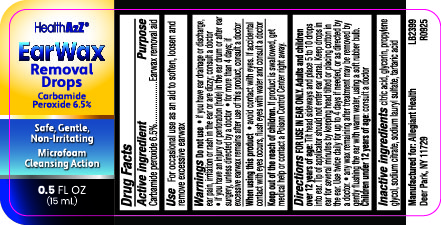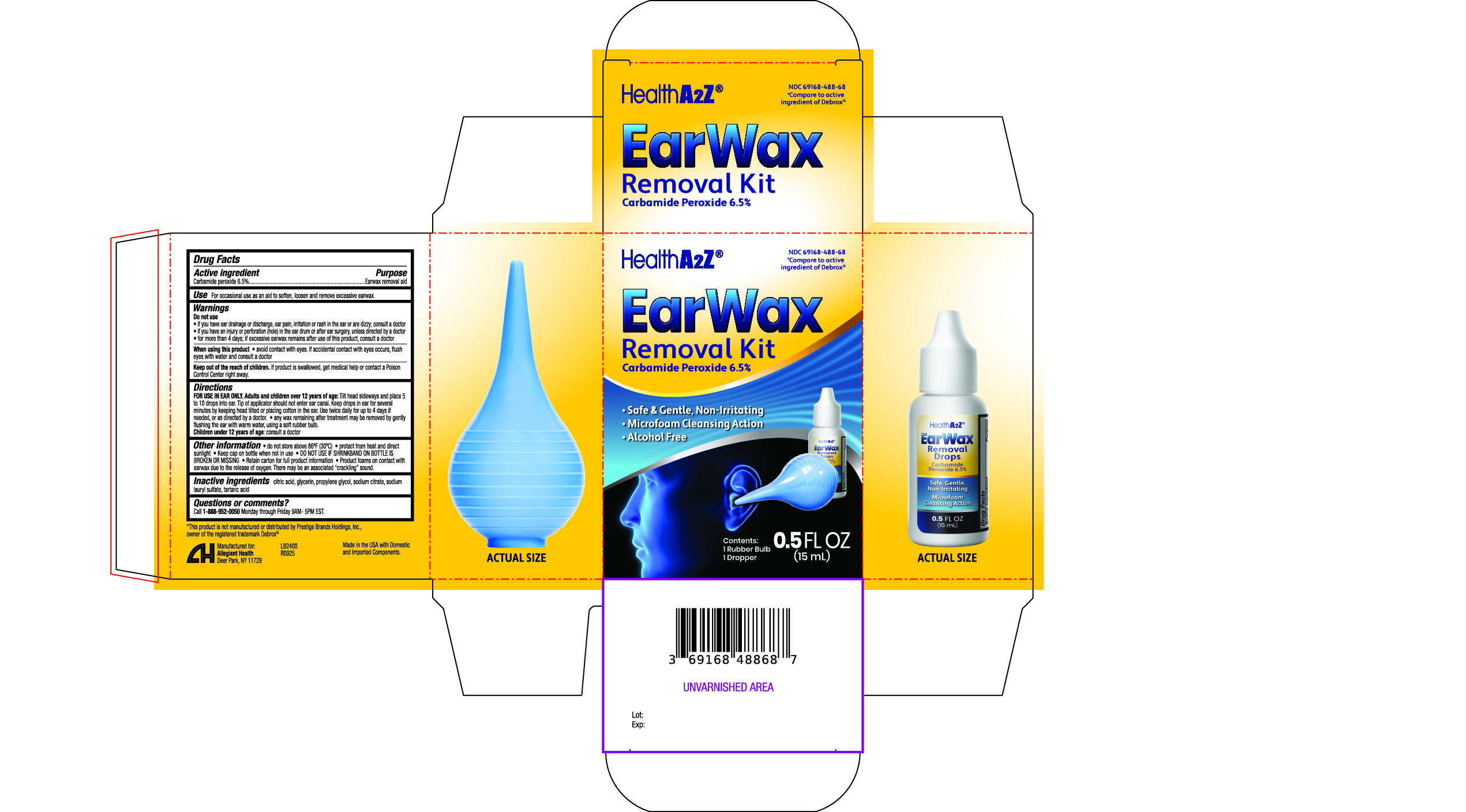 DRUG LABEL: Carbamide peroxide 6.5%
NDC: 69168-488 | Form: SOLUTION/ DROPS
Manufacturer: Allegiant Health
Category: otc | Type: HUMAN OTC DRUG LABEL
Date: 20251028

ACTIVE INGREDIENTS: CARBAMIDE PEROXIDE 65 mg/1 mL
INACTIVE INGREDIENTS: CITRIC ACID; GLYCERIN; PROPYLENE GLYCOL; SODIUM CITRATE; SODIUM LAURYL SULFATE; TARTARIC ACID

488 - Earwax Removal Kit

Active ingredient(s)

Carbamide peroxide 6.5%

Purpose

Earwax removal aid

Use(s)

For occasional use as an aid to soften, loosen and remove excessive earwax.

Warnings

Do not use

- if you have ear drainage or discharge, ear pain, irritation or rash in the ear or are dizzy; consult a doctor
- if you have an injury or perforation (hole) in the ear drum or after ear surgery, unless directed by a doctor
- for more than 4 days; if excessive earwax remains after use of this product, consult a doctor

When using this product

• avoid contact with eyes. If accidental contact with eyes occurs, flush
eyes with water and consult a doctor

Keep out of reach of children

If product is swallowed, get medical help or contact a Poison Control Center right away.

Directions

FOR USE IN EAR ONLY.

Adults and children over 12 years of age: Tilt head sideways and place 5
to 10 drops into ear. Tip of applicator should not enter ear canal. Keep drops in ear for several
minutes by keeping head tilted or placing cotton in the ear. Use twice daily for up to 4 days if
needed, or as directed by a doctor.

• any wax remaining after treatment may be removed by gently
flushing the ear with warm water, using a soft rubber bulb.

Children under 12 years of age: consult a doctor

Other information

• do not store above 86ºF (30ºC)

• protect from heat and direct sunlight

• DO NOT USE IF SHRINKBAND ON BOTTLE IS BROKEN OR MISSING

• Product foams on contact with earwax due to the release of oxygen. There may be an associated “crackling” sound.

• Keep cap on bottle when not in use

• Retain carton for full product information.

Inactive ingredients

citric acid, glycerin, propylene glycol, sodium citrate, sodium lauryl sulfate, tartaric acid

Questions/Comments

Call 1-888-952-0050

(Monday-Friday 9 AM – 5 PM EST)

Principal Display Panel

Earwax label
Earwax carton